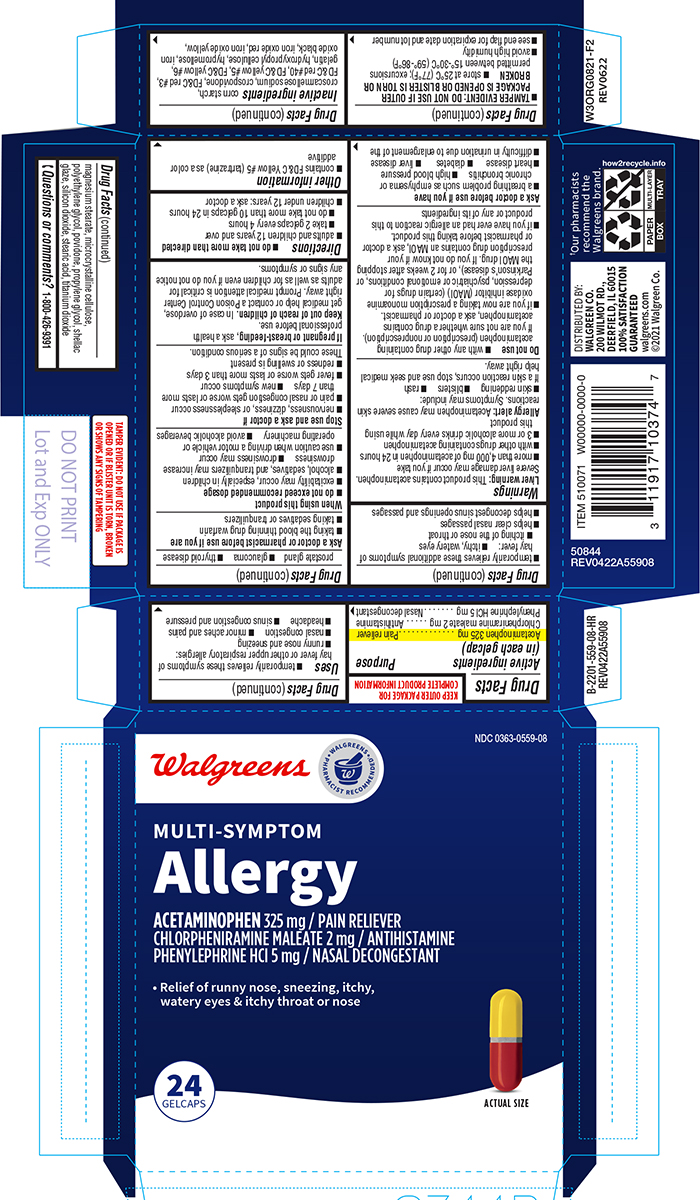 DRUG LABEL: Multi-Symptom Allergy
NDC: 0363-0559 | Form: TABLET, COATED
Manufacturer: Walgreen Company
Category: otc | Type: HUMAN OTC DRUG LABEL
Date: 20250818

ACTIVE INGREDIENTS: ACETAMINOPHEN 325 mg/1 1; CHLORPHENIRAMINE MALEATE 2 mg/1 1; PHENYLEPHRINE HYDROCHLORIDE 5 mg/1 1
INACTIVE INGREDIENTS: STARCH, CORN; CROSCARMELLOSE SODIUM; CROSPOVIDONE, UNSPECIFIED; FD&C RED NO. 3; FD&C RED NO. 40; FD&C YELLOW NO. 5; FD&C YELLOW NO. 6; GELATIN, UNSPECIFIED; HYDROXYPROPYL CELLULOSE, UNSPECIFIED; HYPROMELLOSE, UNSPECIFIED; FERROSOFERRIC OXIDE; FERRIC OXIDE RED; FERRIC OXIDE YELLOW; MAGNESIUM STEARATE; MICROCRYSTALLINE CELLULOSE; POLYETHYLENE GLYCOL, UNSPECIFIED; POVIDONE, UNSPECIFIED; PROPYLENE GLYCOL; SHELLAC; SILICON DIOXIDE; STEARIC ACID; TITANIUM DIOXIDE

Allergy Multi-Symptom

Active ingredients (in each gelcap)

Acetaminophen 325 mg
Chlorpheniramine maleate 2 mg
Phenylephrine HCl 5 mg

Purpose

Pain reliever
Antihistamine
Nasal decongestant

Uses

- temporarily relieves these symptoms of hay fever or other upper respiratory allergies:
  - runny nose and sneezing
  - nasal congestion
  - minor aches and pains
  - headache
  - sinus congestion and pressure
- temporarily relieves these additional symptoms of hay fever:
  - itchy, watery eyes
  - itching of the nose or throat
- helps clear nasal passages
- helps decongest sinus openings and passages

Warnings

Liver warning: This product contains acetaminophen. Severe liver damage may occur if you take

- more than 4,000 mg of acetaminophen in 24 hours
- with other drugs containing acetaminophen
- 3 or more alcoholic drinks every day while using this product

Allergy alert: Acetaminophen may cause severe skin reactions. Symptoms may include:

- skin reddening
- blisters
- rash

If a skin reaction occurs, stop use and seek medical help right away.

Do not use

- with any other drug containing acetaminophen (prescription or nonprescription). If you are not sure whether a drug contains acetaminophen, ask a doctor or pharmacist.
- if you are now taking a prescription monoamine oxidase inhibitor (MAOI) (certain drugs for depression, psychiatric or emotional conditions, or Parkinson’s disease), or for 2 weeks after stopping the MAOI drug. If you do not know if your prescription drug contains an MAOI, ask a doctor or pharmacist before taking this product.
- if you have ever had an allergic reaction to this product or any of its ingredients

Ask a doctor before use if you have

- a breathing problem such as emphysema or chronic bronchitis
- high blood pressure
- heart disease
- diabetes
- liver disease
- difficulty in urination due to enlargement of the prostate gland
- glaucoma
- thyroid disease

Ask a doctor or pharmacist before use if you are

- taking the blood thinning drug warfarin
- taking sedatives or tranquilizers

When using this product

- do not exceed recommended dosage
- excitability may occur, especially in children
- alcohol, sedatives, and tranquilizers may increase drowsiness
- drowsiness may occur
- use caution when driving a motor vehicle or operating machinery
- avoid alcoholic beverages

Stop use and ask a doctor if

- nervousness, dizziness, or sleeplessness occur
- pain or nasal congestion gets worse or lasts more than 7 days
- new symptoms occur
- fever gets worse or lasts more than 3 days
- redness or swelling is present

These could be signs of a serious condition.

If pregnant or breast-feeding,

ask a health professional before use.

Keep out of reach of children.

In case of overdose, get medical help or contact a Poison Control Center right away. Prompt medical attention is critical for adults as well as for children even if you do not notice any signs or symptoms.

Directions

- do not take more than directed
- adults and children 12 years and over
  - take 2 gelcaps every 4 hours
  - do not take more than 10 gelcaps in 24 hours
- children under 12 years: ask a doctor

Other information

- contains FD&C Yellow #5 (tartrazine) as a color additive
- TAMPER EVIDENT: DO NOT USE IF OUTER PACKAGE IS OPENED OR BLISTER IS TORN OR BROKEN
- store at 25°C (77°F); excursions permitted between 15°-30°C (59°-86°F)
- avoid high humidity
- see end flap for expiration date and lot number

Inactive ingredients

corn starch, croscarmellose sodium, crospovidone, FD&C red #3, FD&C red #40, FD&C yellow #5, FD&C yellow #6, gelatin, hydroxypropyl cellulose, hypromellose, iron oxide black, iron oxide red, iron oxide yellow, magnesium stearate, microcrystalline cellulose, polyethylene glycol, povidone, propylene glycol, shellac glaze, silicon dioxide, stearic acid, titanium dioxide

Questions or comments?

1-800-426-9391

Principal display panel

NDC 0363-0559-08

Walgreens

• WALGREENS •
PHARMACIST RECOMMENDED†

MULTI-SYMPTOM
Allergy

ACETAMINOPHEN 325 mg / PAIN RELIEVER
CHLORPHENIRAMINE MALEATE 2 mg / ANTIHISTAMINE
PHENYLEPHRINE HCl 5 mg / NASAL DECONGESTANT

• Relief of runny nose, sneezing, itchy,
watery eyes & itchy throat or nose

24
GELCAPS

ACTUAL SIZE

TAMPER EVIDENT: DO NOT USE IF PACKAGE IS
OPENED OR IF BLISTER UNIT IS TORN, BROKEN
OR SHOWS ANY SIGNS OF TAMPERING

†Our pharmacists
recommend the
Walgreens brand.

50844
REV0422A55908

DISTRIBUTED BY:
WALGREEN CO.
200 WILMOT RD.,
DEERFIELD, IL 60015
100% SATISFACTION
GUARANTEED
walgreens.com
©2021 Walgreen Co.

Walgreens 44-559